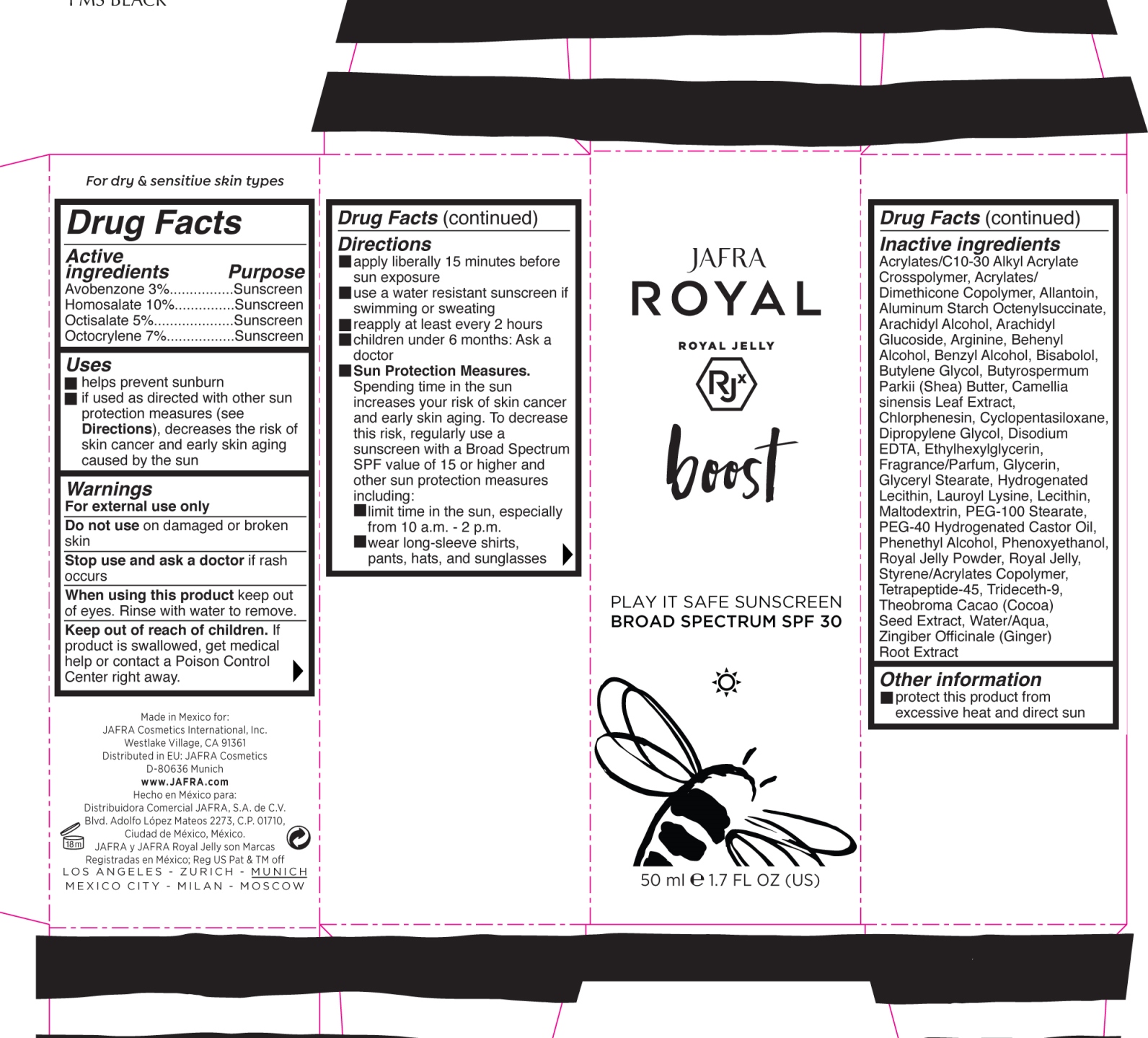 DRUG LABEL: Play It Safe Sunscreen SPF 30
NDC: 68828-281 | Form: LOTION
Manufacturer: Jafra Cosmetics International Inc
Category: otc | Type: HUMAN OTC DRUG LABEL
Date: 20200611

ACTIVE INGREDIENTS: HOMOSALATE 10 g/100 mL; OCTISALATE 5 g/100 mL; AVOBENZONE 3 g/100 mL; OCTOCRYLENE 7 g/100 mL
INACTIVE INGREDIENTS: BENZYL ALCOHOL; SHEA BUTTER; COCOA; GINGER; DOCOSANOL; LAUROYL LYSINE; LECITHIN, SOYBEAN; MALTODEXTRIN; PEG-100 STEARATE; POLYOXYL 40 HYDROGENATED CASTOR OIL; ARGININE; DIPROPYLENE GLYCOL; ALLANTOIN; ALUMINUM STARCH OCTENYLSUCCINATE; ARACHIDYL ALCOHOL; LEVOMENOL; BUTYLENE GLYCOL; GREEN TEA LEAF; CHLORPHENESIN; PHENYLETHYL ALCOHOL; GLYCERIN; GLYCERYL MONOSTEARATE; HYDROGENATED SOYBEAN LECITHIN; PHENOXYETHANOL; ROYAL JELLY; TRIDECETH-9; WATER; ETHYLHEXYLGLYCERIN; CYCLOMETHICONE 5; EDETATE DISODIUM

Play It Safe Sunscreen Broad Spectrum SPF 30

Active ingredients Purpose
Avobenzone 3%................Sunscreen
Homosalate 10%...............Sunscreen
Octisalate 5%....................Sunscreen
Octocrylene 7%.................Sunscreen

Uses

- helps prevent sunburn
- if used as directed with other sun protection measures (see Directions), decreases the risk of skin cancer and early skin aging caused by the sun

- Stop use and ask a doctor if rash occurs

Stop use and ask a doctor if rash occurs

Warnings
For external use only
Do not use on damaged or broken skin
When using this product keep out of eyes. Rinse with water to remove.

Directions

- apply liberally 15 minutes before sun exposure
- use a water resistant sunscreen if swimming or sweating
- reapply at least every 2 hours
- children under 6 months: Ask a doctor

Sun Protection Measures.
Spending time in the sun increases your risk of skin cancer and early skin aging. To decrease this risk, regularly use a sunscreen with a Broad Spectrum SPF value of 15 or higher and other sun protection measures including:

- limit time in the sun, especially from 10 a.m. - 2 p.m.
- wear long-sleeve shirts, pants, hats, and sunglasses

Inactive ingredients
Acrylates/C10-30 Alkyl Acrylate Crosspolymer, Acrylates/ Dimethicone Copolymer, Allantoin, Aluminum Starch Octenylsuccinate, Arachidyl Alcohol, Arachidyl Glucoside, Arginine, Behenyl Alcohol, Benzyl Alcohol, Bisabolol, Butylene Glycol, Butyrospermum Parkii (Shea) Butter, Camellia sinensis Leaf Extract, Chlorphenesin, Cyclopentasiloxane, Dipropylene Glycol, Disodium EDTA, Ethylhexylglycerin, Fragrance/Parfum, Glycerin, Glyceryl Stearate, Hydrogenated Lecithin, Lauroyl Lysine, Lecithin, Maltodextrin, PEG-100 Stearate, PEG-40 Hydrogenated Castor Oil, Phenethyl Alcohol, Phenoxyethanol, Royal Jelly Powder, Royal Jelly, Styrene/Acrylates Copolymer, Tetrapeptide-45, Trideceth-9, Theobroma Cacao (Cocoa) Seed Extract, Water/Aqua, Zingiber Officinale (Ginger) Root Extract

PACKAGE LABEL

boost Play It Safe Sunscreen

Broad Spectrum SPF 30